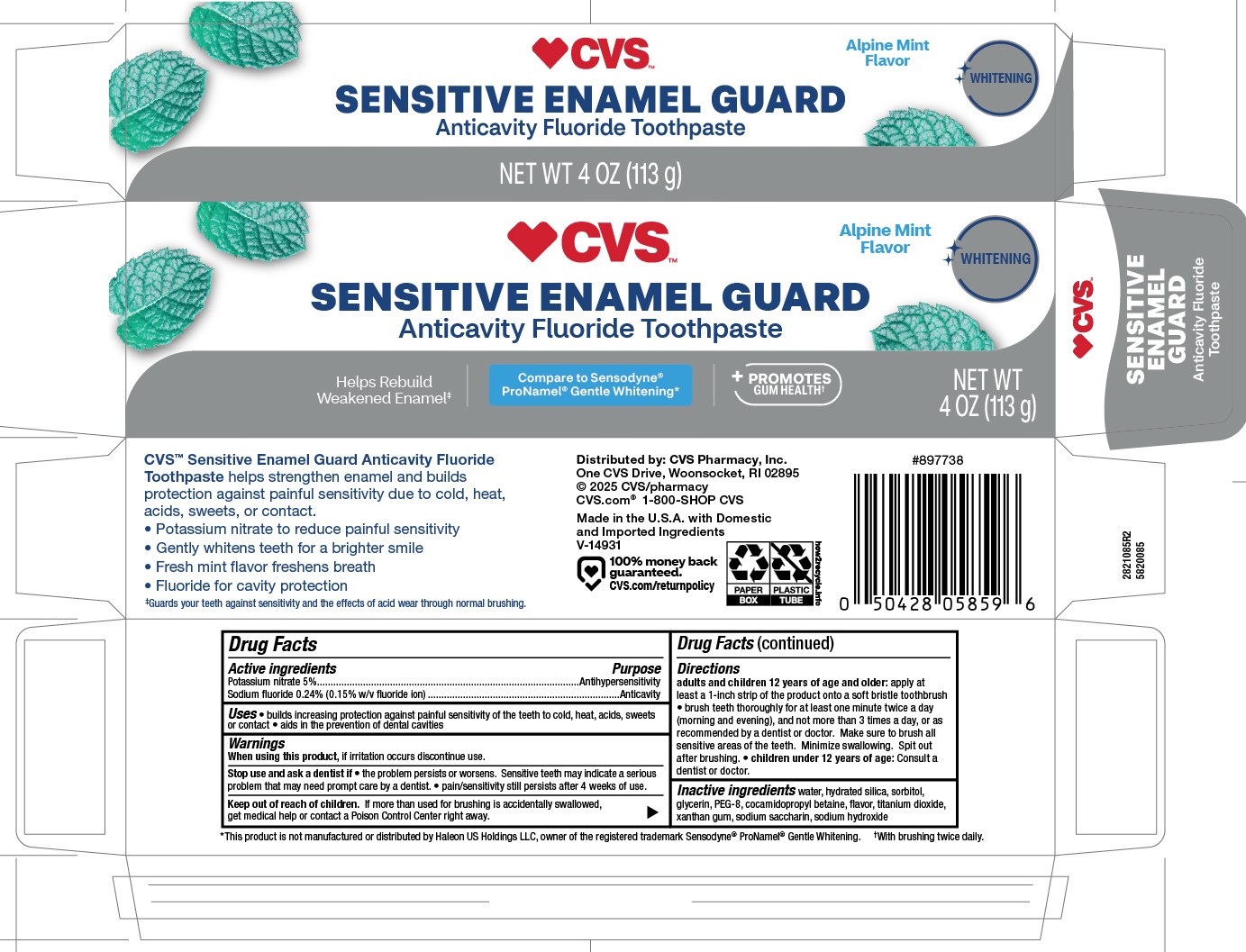 DRUG LABEL: CVS Pharmacy
NDC: 59779-815 | Form: PASTE, DENTIFRICE
Manufacturer: CVS Pharmacy
Category: otc | Type: HUMAN OTC DRUG LABEL
Date: 20251121

ACTIVE INGREDIENTS: SODIUM FLUORIDE 0.15 g/100 g; POTASSIUM NITRITE 5 g/100 g
INACTIVE INGREDIENTS: SORBITOL; TITANIUM DIOXIDE; GLYCERIN; SACCHARIN SODIUM; WATER; SODIUM HYDROXIDE; XANTHAN GUM; COCAMIDOPROPYL BETAINE; POLYETHYLENE GLYCOL 400; HYDRATED SILICA

5820085, 5820164 CVS Sens Enamel Guard Mint

Active ingredients

Potassium Nitrate 5%......................................................................Antihypersensitivity

Sodium Fluoride 0.24% (0.15% w/v fluoride ion)...........................................Anticavity

Uses

- builds increasing protection against painful sensitivity of the teeth to cold, heat, acids, sweets or contact
- aids in the prevention of dental caviites

Directions

Adults and children 12 years of age and older: apply at least a 1-inch strip of the product onto a soft bristle toothbruch.

- brush teeth thorughly for at least one minute for at least twice a day (morning and evening), and not more than 3 times a day, or as directed by a dentist or doctor. Make sure to brush all sensitive areas of the teeth. Minimize swallowing. Spit out after brushing.
- children under 12 years of age: Consult a dentist or doctor.

When using this product, if irritaiton occurs discontinue use.

Keep out of reach of children. If more than used for brushing is accidentally swallowed, get medical help of contact a Posion Control Center right away.

Stop use and ask a dentist if

- the problem persists or worsens. Sensitive teeth may indicate a serious problem that may need prompt care by a dentist.
- pain/sensitivity still persists after 4 weeks of use.

Other Information

Store in a cool dry place. Keep tube capped when not in use.

Inactive ingredients

water, hydrated silica, sorbitol, glycerin, PEG-8, cocamidpropyl betaine, flavor, titanium dioxide, xanthan gum, sodium saccharin, sodium hydroxide

DOSAGE AND ADMINISTRATION

Adults and children 12 years of age and older: apply at least a 1-inch strip of the product onto a soft bristle toothbruch.